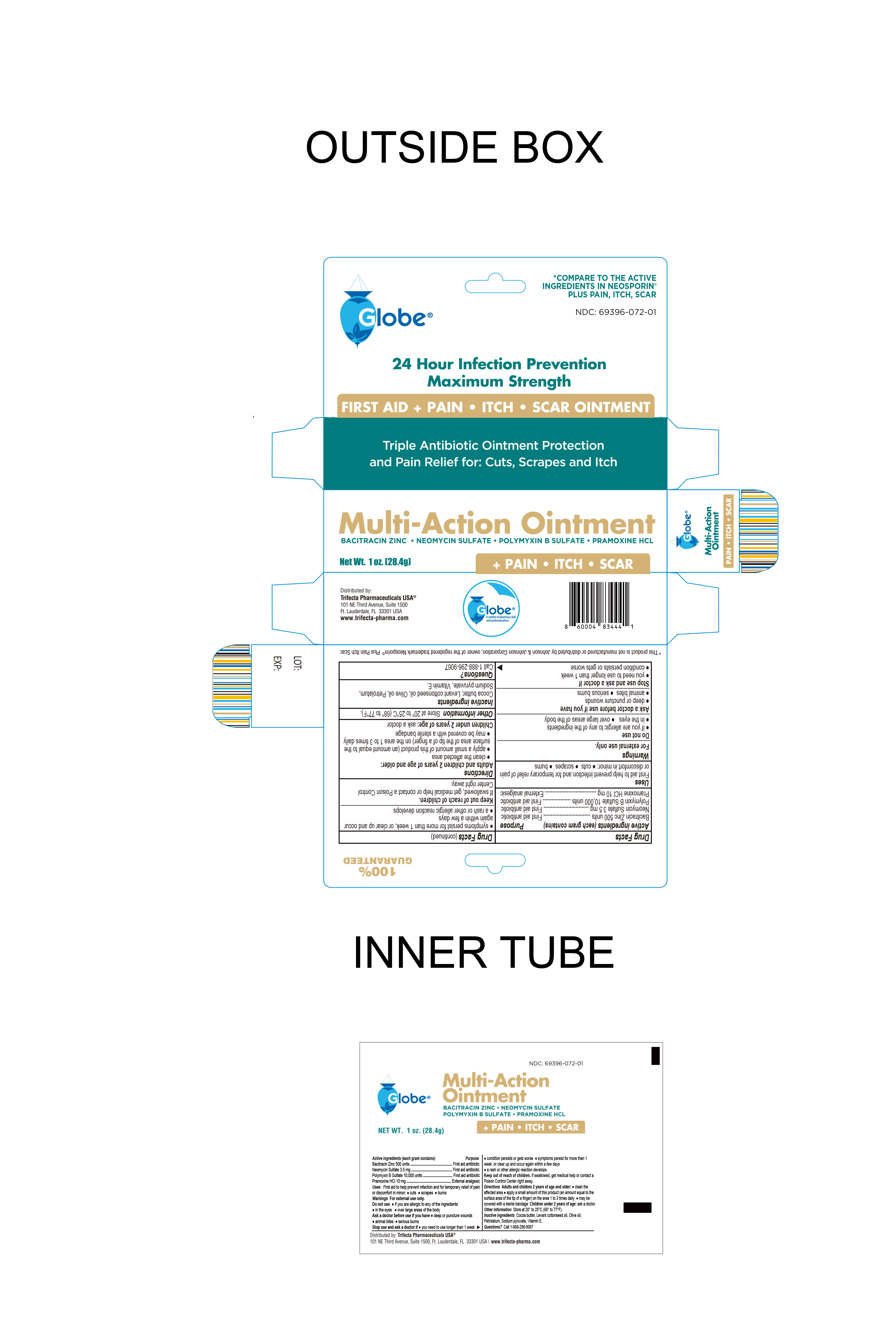 DRUG LABEL: Multi Action
NDC: 69396-072 | Form: OINTMENT
Manufacturer: Trifecta Pharmaceutical USA LLC
Category: otc | Type: HUMAN OTC DRUG LABEL
Date: 20250513

ACTIVE INGREDIENTS: POLYMYXIN B SULFATE 10000 [USP'U]/1 g; BACITRACIN ZINC 500 [USP'U]/1 g; NEOMYCIN SULFATE 3.5 mg/1 g; PRAMOXINE HYDROCHLORIDE 10 mg/1 g
INACTIVE INGREDIENTS: SODIUM PYRUVATE; ALPHA-TOCOPHEROL; OLIVE OIL; LEVANT COTTONSEED OIL; COCOA BUTTER; PETROLATUM

Multi-Action Ointment

Active Ingredient

Bacitracin Zinc 500 Units

Purpose

First Aid Antibiotic

Active Ingredient

Neomycin Sulfate 3.5mg

Purpose

First Aid Antibiotic

Active Ingredient

Polymyxin B Sulfate 10,000 Units

Purpose

First Aid Antibiotic

Active Ingredient

Pramoxine HCL 10mg

Purpose

External Analgesic

Uses

First Aid to help prevent infection in and for temporary relief of pain or discomfort in minor cuts, scrapes and burns.

Warnings

For external use only. Do not use:

- If you are allergic to any of the ingredients
- in the eyes
- on large areas of the body

Ask a Doctor before Use

Ask Doctor before use if you have:

- Deep or puncture wounds
- Animal bites
- Serious burns

Stop Use and ask a Doctor if:

- You need to use longer than 1 week
- Condition persists or gets worse
- Symptoms persists for more than 1 week or clear up and occur again within a few days
- A rash or other allergic reaction develops

Keep out of Reach of Children

If Swallowed, get medical help or contact a Poison Control Center right away

Directions

Adults and children 2 years and older:

- Clean the affected area
- Apply a small amount of this product (an amount equal to the surface area of the tip of a finger) on the area 1 to 3 times daily
- May be covered with a sterile bandage

Children under 2 years: ask a doctor

Other Information

- Store at 20° to 25°C (68° to 77°F)

Inactive Ingredient:

Cocoa Butter, Levant Cottonseed Oil, Olive Oil, Petrolatum, Sodium pyruvate, vitamin E

Questions?

Call 1-888-296-9067 Weekdays 9AM - 5PM EST

Other Information

Distributed By

Trifecta Pharmaceuticals USA®

101 NE Third Avenue, Suite 1500

Ft. Lauderdale, FL. 33301 USA

www.trifecta-pharma.com

This product is not manufactured or distributed by Johnson & Johnson Corporation, owner of the registered trademark Neosporin® Plus Pain Itch Scar.